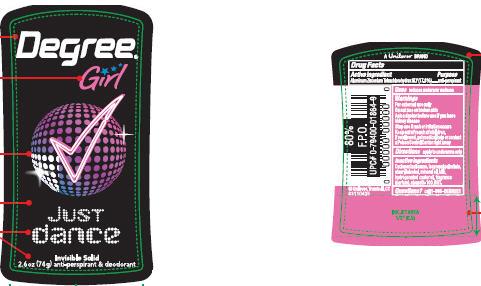 DRUG LABEL: Degree Girl Just Dance
NDC: 64942-1089 | Form: STICK
Manufacturer: Conopco Inc. d/b/a Unilever
Category: otc | Type: HUMAN OTC DRUG LABEL
Date: 20100223

ACTIVE INGREDIENTS: Aluminum Zirconium Tetrachlorohydrex GLY 17.8 g/100 g

Degree Girl Just Dance Antiperspirant and Deodorant back and front PACKAGE LABEL.PRINCIPAL DISPLAY PANEL and Drug Facts

Active ingredient Purpose

Aluminum Zirconium Tetrachlorohydrex GLY (17.8%)...................anti-perspirant

Warning
For external use only

Do not use on broken skin

Ask a doctor before use if you havekidney disease

Keep out of reach of children.

If swallowed, get medical help or contact a Poison Control Center right away

Stop use if rash or irritation occurs.

Keep out of reach of children.
If swallowed, get medical help or contact a Poison Control Center right away

Inactive ingredients

Cyclopentasiloxane, Isopropyl Palmitate, Stearyl Alcohol, Mineral Oil, Talc, Hydrogenated Castor Oil, Fragrance (Parfum) , Steareth-100, BHT.

Questions? call 1-866-DEGREE1

PACKAGE LABEL

PDP 2.6 oz